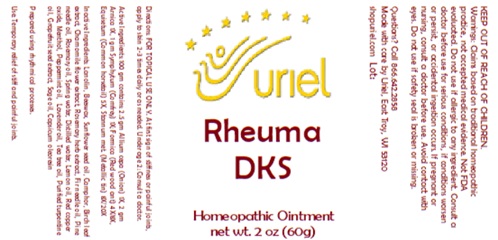 DRUG LABEL: Rheuma DKS
NDC: 48951-8428 | Form: OINTMENT
Manufacturer: Uriel Pharmacy Inc.
Category: homeopathic | Type: HUMAN OTC DRUG LABEL
Date: 20250122

ACTIVE INGREDIENTS: EQUISETUM ARVENSE TOP 5 [hp_X]/1 g; FORMICA RUFA 4 [hp_X]/1 g; ONION 1 [hp_X]/1 g; ARNICA MONTANA FLOWER 1 [hp_X]/1 g; COMFREY ROOT 1 [hp_X]/1 g; TIN 8 [hp_X]/1 g
INACTIVE INGREDIENTS: CAPSICUM OLEORESIN; CHAMOMILE; LANOLIN; YELLOW WAX; BETULA PUBESCENS LEAF; ROSEMARY; SUNFLOWER OIL; CAMPHOR (NATURAL); ABIES SIBIRICA LEAF OIL; PINE NEEDLE OIL (PINUS SYLVESTRIS); ROSEMARY OIL; WATER; LEMON OIL; CUPROUS OXIDE; MENTHOL; PEPPERMINT OIL; LAVENDER OIL; TURPENTINE OIL; SAGE OIL; CITRUS PARADISI SEED; TEA TREE OIL

Rheuma DKS

INDICATIONS AND USAGE

Directions: FOR TOPICAL USE ONLY.

DOSAGE AND ADMINISTRATION

At first sign of stiffness or painful joints, apply to skin 2-3 times daily or as needed. Under age 2: Consult a doctor.

ACTIVE INGREDIENT

Active Ingredients: 100 gm contains: 2.5 gm Allium cepa (Onion) 1X, 2 gm Arnica 1X, 1 gm Symphytum (Comfrey) 1X; Formica (Red wood ant) 4X/8X, Equisetum (Common horsetail) 5X, Stannum met. (Metallic tin) 8X/20X

INACTIVE INGREDIENT

Inactive Ingredients: Lanolin, Beeswax, Sunflower seed oil, Camphor, Birch leaf extract, Chamomile flower extract, Rosemary herb extract, Fir needle oil, Pine needle oil, Rosemary oil, Spring water, Lemon oil, Red copper oxide, Menthol, Peppermint oil, Lavender oil, Tea tree oil, Purified turpentine oil, Grapefruit seed extract, Sage oil, Capsicum oleoresin

Prepared using rhythmical processses.

PURPOSE

Use: Temporary relief of stiff and painful joints.

KEEP OUT OF REACH OF CHILDREN.

WARNINGS

Warnings: Claims based on traditional homeopathic practice, not accepted medical evidence. Not FDA evaluated. Do not use if allergic to any ingredient. Consult a doctor before use for serious conditions, if conditions worsen or persist, or accidental ingestion occurs. If pregnant or nursing, consult a doctor before use. Avoid contact with eyes. Do not use if safety seal is broken or missing.

QUESTIONS

Questions? Call 866.642.2858 Made with care by Uriel, East Troy, WI 53120 shopuriel.com Lot: